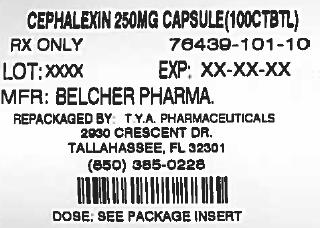 DRUG LABEL: Lithium Carbonate
NDC: 64725-2527 | Form: CAPSULE, GELATIN COATED
Manufacturer: TYA Pharmaceuticals
Category: prescription | Type: HUMAN PRESCRIPTION DRUG LABEL
Date: 20140310

ACTIVE INGREDIENTS: LITHIUM CARBONATE 300 mg/1 1
INACTIVE INGREDIENTS: FD&C RED NO. 40; GELATIN; SODIUM LAURYL SULFATE; TALC; TITANIUM DIOXIDE; FERROSOFERRIC OXIDE; POVIDONE K30; SHELLAC

LITHIUM CARBONATE Tablets USP, LITHIUM CARBONATE Capsules USP, LITHIUM Oral Solution USP

Rx only

WARNING

BOXED WARNING

Lithium toxicity is closely related to serum lithium levels, and can occur at doses close to therapeutic levels. Facilities for prompt and accurate serum lithium determinations should be available before initiating therapy (see). DOSAGE AND ADMINISTRATION

DESCRIPTION

Each tablet for oral administration contains:

Lithium Carbonate . . . . . . . . . . 300 mg

Each capsule for oral administration contains:

Lithium Carbonate . . . . . . . . . . 150 mg, 300 mg or 600 mg

Each 5 mL of solution for oral administration contains:

Lithium ion (Li+) . . . . . . . . . . 8 mEq

(equivalent to amount of lithium in 300 mg of lithium carbonate), alcohol 0.3% v/v.

Inactive Ingredients

The tablets contain calcium stearate, microcrystalline cellulose, povidone, sodium lauryl sulfate, and sodium starch glycolate. The capsules contain FD&C Red No. 40, gelatin, sodium lauryl sulfate, talc, titanium dioxide, and the imprinting ink contains FD&C Blue No. 2, FD&C Yellow No. 6, FD&C Red No. 40, iron oxide, polyvinly pyrrolidone, shellac. The solution contains citric acid, raspberry blend, sodium benzoate, sorbitol and water.

Lithium Oral Solution is a palatable oral dosage form of lithium ion. It is prepared in solution from lithium hydroxide and citric acid in a ratio approximately di-lithium citrate.

Lithium is an element of the alkali-metal group with atomic number 3, atomic weight 6.94, and an emission line at 671 nm on the flame photometer.

The empirical formula for Lithium Citrate is C H Li O ; molecular weight 209.92. Lithium acts as an antimanic.6537

Lithium Carbonate is a white, light, alkaline powder with molecular formula Li CO and molecular weight 73.89.23

CLINICAL PHARMACOLOGY

Preclinical studies have shown that lithium alters sodium transport in nerve and muscle cells and effects a shift toward intraneuronal metabolism of catecholamines, but the specific biochemical mechanism of lithium action in mania is unknown.

INDICATIONS AND USAGE

Lithium is indicated in the treatment of manic episodes of Bipolar Disorder. Bipolar Disorder, Manic (DSM-III) is equivalent to Manic Depressive illness, Manic, in the older DSM-II terminology.

Lithium is also indicated as a maintenance treatment for individuals with a diagnosis of Bipolar Disorder. Maintenance therapy reduces the frequency of manic episodes and diminishes the intensity of those episodes which may occur.

Typical symptoms of mania include pressure of speech, motor hyperactivity, reduced need for sleep, flight of ideas, grandiosity, elation, poor judgment, aggressiveness, and possibly hostility. When given to a patient experiencing a manic episode, lithium may produce a normalization of symptomatology within 1 to 3 weeks.

CONTRAINDICATIONS

Lithium should generally not be given to patients with significant renal or cardiovascular disease, severe debilitation or dehydration, or sodium depletion, and to patients receiving diuretics, since the risk of lithium toxicity is very high in such patients. If the psychiatric indication is life-threatening, and if such a patient fails to respond to other measures, lithium treatment may be undertaken with extreme caution, including daily serum lithium determinations and adjustment to the usually low doses ordinarily tolerated by these individuals. In such instances, hospitalization is a necessity.

WARNINGS

Lithium toxicity is closely related to serum lithium levels, and can occur at doses close to therapeutic levels (see). DOSAGE AND ADMINISTRATION

Unmasking of Brugada Syndrome

There have been postmarketing reports of a possible association between treatment with lithium and the unmasking of Brugada Syndrome. Brugada Syndrome is a disorder characterized by abnormal electrocardiographic (ECG) findings and a risk of sudden death. Lithium should generally be avoided in patients with Brugada Syndrome or those suspected of having Brugada Syndrome. Consultation with a cardiologist is recommended if: (1) treatment with lithium is under consideration for patients suspected of having Brugada Syndrome or patients who have risk factors for Brugada Syndrome, e.g., unexplained syncope, a family history of Brugada Syndrome, or a family history of sudden unexplained death before the age of 45 years, (2) patients who develop unexplained syncope or palpitations after starting lithium therapy.

Pregnancy

Lithium may cause fetal harm when administered to a pregnant woman. There have been reports of lithium having adverse effects on nidations in rats, embryo viability in mice, and metabolism in-vitro of rat testis and human spermatozoa have been attributed to lithium, as have teratogenicity in submammalian species and cleft palates in mice. Studies in rats, rabbits and monkeys have shown no evidence of lithium-induced teratology. Data from lithium birth registries suggest an increase in cardiac and other anomalies, especially Ebstein’s anomaly. If the patient becomes pregnant while taking lithium, she should be apprised of the potential risk to the fetus. If possible, lithium should be withdrawn for at least the first trimester unless it is determined that this would seriously endanger the mother.

Lithium-Induced Renal Effects

Chronic lithium therapy may be associated with diminution of renal concentrating ability, occasionally presenting as nephrogenic diabetes insipidus, with polyuria and polydipsia. Such patients should be carefully managed to avoid dehydration with resulting lithium retention and toxicity. This condition is usually reversible when lithium is discontinued.

Morphologic changes with glomerular and interstitial fibrosis and nephron-atrophy have been reported in patients on chronic lithium therapy. Morphologic changes have also been seen in bipolar patients never exposed to lithium. The relationship between renal functional and morphologic changes and their association with lithium therapy has not been established.

When kidney function is assessed, for baseline data prior to starting lithium therapy or thereafter, routine urinalysis and other tests may be used to evaluate tubular function (e.g., urine specific gravity or osmolality following a period of water deprivation, or 24-hour urine volume) and glomerular function (e.g., serum creatinine or creatinine clearance). During lithium therapy, progressive or sudden changes in renal function, even within the normal range, indicate the need for reevaluation of treatment.

PRECAUTIONS

General

The ability to tolerate lithium is greater during the acute manic phase and decreases when manic symptoms subside (see). DOSAGE AND ADMINISTRATION

The distribution space of lithium approximates that of total body water. Lithium is primarily excreted in urine with insignificant excretion in feces. Renal excretion of lithium is proportional to its plasma concentration. The half-life of elimination of lithium is approximately 24 hours. Lithium decreases sodium reabsorption by the renal tubules which could lead to sodium depletion. Therefore, it is essential for the patient to maintain a normal diet, including salt, and an adequate fluid intake (2500-3000 mL) at least during the initial stabilization period. Decreased tolerance to lithium has been reported to ensue from protracted sweating or diarrhea and, if such occur, supplemental fluid and salt should be administered.

In addition to sweating and diarrhea, concomitant infection with elevated temperatures may also necessitate a temporary reduction or cessation of medication.

Previously existing underlying thyroid disorders do not necessarily constitute a contraindication to lithium treatment; where hypothyroidism exists, careful monitoring of thyroid function during lithium stabilization and maintenance allows for correction of changing thyroid parameters, if any. Where hypothyroidism occurs during lithium stabilization and maintenance, supplemental thyroid treatment may be used.

Information for the Patients

A condition known as Brugada Syndrome may pre-exist and be unmasked by lithium therapy. Brugada Syndrome is a heart disorder characterized by abnormal electrocardiographic (ECG) findings and risk of sudden death. Patients should be advised to seek immediate emergency assistance if they experience fainting, lightheadedness, abnormal heart beats, or shortness of breath.

Outpatients and their families should be warned that the patient must discontinue lithium therapy and contact his physician if such clinical signs of lithium toxicity as diarrhea, vomiting, tremor, mild ataxia, drowsiness, or muscular weakness occur.

Lithium may impair mental and/or physical abilities. Caution patients about activities requiring alertness (e.g., operating vehicles or machinery).

Drug Interactions

Combined Use of Haloperidol and Lithium.

An encephalopathic syndrome (characterized by weakness, lethargy, fever, tremulousness and confusion, extrapyramidal symptoms, leucocytosis, elevated serum enzymes, BUN and FBS) followed by irreversible brain damage has occurred in a few patients treated with lithium plus haloperidol. A causal relationship between these events and the concomitant administration of lithium and haloperidol has not been established; however, patients receiving such combined therapy should be monitored closely for early evidence of neurological toxicity and treatment discontinued promptly if such signs appear.

The possibility of similar adverse interactions with other antipsychotic medication exists.

Lithium may prolong the effects of neuromuscular blocking agents. Therefore, neuromuscular blocking agents should be given with caution to patients receiving lithium.

Caution should be used when lithium and diuretics or angiotensin converting enzyme (ACE) inhibitors are used concomitantly because sodium loss may reduce the renal clearance of lithium and increase serum lithium levels with risk of lithium toxicity. When such combinations are used, the lithium dosage may need to be decreased, and more frequent monitoring of lithium plasma levels is recommended.

Non-Steroidal Anti-Inflammatory Drugs (NSAIDS)

Lithium levels should be closely monitored when patients initiate or discontinue NSAID use. In some cases, lithium toxicity has resulted from interactions between an NSAID and lithium. Indomethacin and piroxicam have been reported to increase significantly steady-state plasma lithium concentrations. There is also evidence that other nonsteroidal anti-inflammatory agents, including the selective cyclooxygenase-2 (COX-2) inhibitors, have the same effect. In a study conducted in healthy subjects, mean steady-state lithium plasma levels increased approximately 17% in subjects receiving lithium 450 mg BID with celecoxib 200 mg BID as compared to subjects receiving lithium alone.

Pregnancy, Teratogenic Effects

: Pregnancy Category D

See section. WARNINGS

Nursing Mothers

Lithium is excreted in human milk. Nursing should not be undertaken during lithium therapy except in rare and unusual circumstances where, in the view of the physician, the potential benefits to the mother outweigh possible hazards to the child.

Usage in Children

Since information regarding the safety and effectiveness of lithium in children under 12 years of age is not available, its use in such patients is not recommended at this time. There has been a report of a transient syndrome of acute dystonia and hyperreflexia occurring in a 15 kg child who ingested 300 mg of lithium carbonate.

ADVERSE REACTIONS

Lithium Toxicity

The likelihood of toxicity increases with increasing serum lithium levels. Serum lithium levels greater than 1.5 mEq/l carry a greater risk than lower levels. However, patients sensitive to lithium may exhibit toxic signs at serum levels below 1.5 mEq/l.

Diarrhea, vomiting, drowsiness, muscular weakness and lack of coordination may be early signs of lithium toxicity, and can occur at lithium levels below 2.0 mEq/l. At higher levels, giddiness, ataxia, blurred vision, tinnitus and a large output of dilute urine may be seen. Serum lithium levels above 3.0 mEq/l may produce a complex clinical picture involving multiple organs and organ systems. Serum lithium levels should not be permitted to exceed 2.0 mEq/l during the acute treatment phase.

Fine hand tremor, polyuria and mild thirst may occur during initial therapy for the acute manic phase, and may persist throughout treatment. Transient and mild nausea and general discomfort may also appear during the first few days of lithium administration.

These side effects are an inconvenience rather than a disabling condition, and usually subside with continued treatment or a temporary reduction or cessation of dosage. If persistent, a cessation of dosage is indicated.

The following adverse reactions have been reported and do not appear to be directly related to serum lithium levels.

: Tremor, muscle hyperirritability (fasciculations, twitching, clonic movements of whole limbs), ataxia, choreo-athetotic movements, hyperactive deep tendon reflexes. Neuromuscular

: Blackout spells, epileptiform seizures, slurred speech, dizziness, vertigo, incontinence of urine or feces, somnolence, psychomotor retardation, restlessness, confusion, stupor, coma, acute dystonia, downbeat nystagmus. Central Nervous System

: Cardiac arrhythmia, hypotension, peripheral circulatory collapse, sinus node dysfunction with severe bradycardia (which may result in syncope), unmasking of Brugada Syndrome (See and). Cardiovascular WARNINGS: Unmasking of Brugada Syndrome PRECAUTIONS: Information for the Patients

: Cases of pseudotumor cerebri (increased intracranial pressure and papilledema) have been reported with lithium use. If undetected, this condition may result in enlargement of the blind spot, constriction of visual fields and eventual blindness due to optic atrophy. Lithium should be discontinued, if clinically possible, if this syndrome occurs. Neurological

: Anorexia, nausea, vomiting, diarrhea. Gastrointestinal

: Albuminuria, oliguria, polyuria, glycosuria. Genitourinary

: Drying and thinning of hair, anesthesia of skin, chronic folliculitis, xerosis cutis, alopecia and exacerbation of psoriasis. Dermatologic

: Blurred vision, dry mouth. Autonomic Nervous System

: Euthyroid goiter and/or hypothyroidism (including myxedema) accompanied by lower T3 and T4. Iodine 131 uptake may be elevated. (See). Paradoxically, rare cases of hyperthyroidism have been reported. Thyroid Abnormalities PRECAUTIONS

: Diffuse slowing, widening of frequency spectrum, potentiation and disorganization of background rhythm. EEG Changes

: Reversible flattening, isoelectricity or inversion of T-waves. EKG Changes

: Fatigue, lethargy, transient scotomata, dehydration, weight loss, tendency to sleep. Miscellaneous

: Transient electroencephalographic and electrocardiographic changes, leucocytosis, headache, diffuse non-toxic goiter with or without hypothyroidism, transient hyperglycemia, generalized pruritus with or without rash, cutaneous ulcers, albuminuria, worsening of organic brain syndromes, excessive weight gain, edematous swelling of ankles or wrists, and thirst or polyuria, sometimes resembling diabetes insipidus, and metallic taste. Miscellaneous Reactions Unrelated to Dosage are

A single report has been received of the development of painful discoloration of fingers and toes and coldness of the extremities within one day of the starting of treatment of lithium. The mechanism through which these symptoms (resembling Raynaud’s Syndrome) developed is not known. Recovery followed discontinuance.

OVERDOSAGE

The toxic levels for lithium are close to the therapeutic levels. It is therefore important that patients and their families be cautioned to watch for early symptoms and to discontinue the drug and inform the physician should they occur. Toxic symptoms are listed in detail under . ADVERSE REACTIONS

Treatment

No specific antidote for lithium poisoning is known. Early symptoms of lithium toxicity can usually be treated by reduction of cessation of dosage of the drug and resumption of the treatment at a lower dose after 24 to 48 hours. In severe cases of lithium poisoning, the first and foremost goal of treatment consists of elimination of this ion from the patient.

Treatment is essentially the same as that used in barbiturate poisoning: 1) gastric lavage, 2) correction of fluid and electrolyte imbalance and 3) regulation of kidney functioning. Urea, mannitol, and aminophylline all produce significant increases in lithium excretion. Hemodialysis is an effective and rapid means of removing the ion from the severely toxic patient. Infection prophylaxis, regular chest X-rays, and preservation of adequate respiration are essential.

DOSAGE AND ADMINISTRATION

Acute Mania

Optimal patient response to Lithium Carbonate usually can be established and maintained with 600 mg t.i.d. Optimal patient response to Lithium Oral Solution usually can be established and maintained with 10 mL (2 full teaspoons) (16 mEq of lithium) t.i.d. Such doses will normally produce an effective serum lithium level ranging between 1.0 and 1.5 mEq/l. Dosage must be individualized according to serum levels and clinical response. Regular monitoring of the patient’s clinical state and of serum lithium levels is necessary. Serum levels should be determined twice per week during the acute phase, and until the serum level and clinical condition of the patient have been stabilized.

Long-Term Control

The desirable serum lithium levels are 0.6 to 1.2 mEq/l. Dosage will vary from one individual to another, but usually 300 mg of Lithium Carbonate t.i.d. or q.i.d., or 5 mL (1 full teaspoon) (8 mEq of Lithium) of Lithium Oral Solution t.i.d. or q.i.d. will maintain this level. Serum lithium levels in uncomplicated cases receiving maintenance therapy during remission should be monitored at least every two months.

Patients abnormally sensitive to lithium may exhibit toxic signs at serum levels of 1.0 to 1.5 mEq/l. Elderly patients often respond to reduced dosage, and may exhibit signs of toxicity at serum levels ordinarily tolerated by other patients.

N.B.

Blood samples for serum lithium determination should be drawn immediately prior to the next dose when lithium concentrations are relatively stable (i.e., 8-12 hours after the previous dose). Total reliance must not be placed on serum levels alone. Accurate patient evaluation requires both clinical and laboratory analysis.

HOW SUPPLIED

Lithium Carbonate Tablets USP

300 mg white, scored tablets (Identified 54 452)

NDC 0054-8528-25: Unit dose, 10 tablets per strip, 10 strips per shelf pack, 10 shelf packs per shipper.

(For Institutional Use Only).

NDC 0054-4527-25: Bottles of 100 tablets.

NDC 0054-4527-31: Bottles of 1000 tablets.

Lithium Carbonate Capsules USP

150 mg white opaque colored capsules (size 4)

(Identified 54 213).

NDC 0054-8526-25: Unit dose, 10 capsules per strip, 10 strips per shelf pack, 10 shelf packs per shipper.

(For Institutional Use Only).

NDC 0054-2526-25: Bottles of 100 capsules.

300 mg flesh-colored capsules (size 2)

(Identified 54 463).

NDC 0054-8527-25: Unit dose, 10 capsules per strip, 10 strips per shelf pack, 10 shelf packs per shipper.

(For Institutional Use Only).

NDC 0054-2527-25: Bottles of 100 capsules.

NDC 0054-2527-31: Bottles of 1000 capsules.

600 mg white opaque/flesh colored capsules

(size 0) (Identified 54 702).

NDC 0054-8531-25: Unit dose, 10 capsules per strip, 10 strips per shelf pack, 10 shelf packs per shipper.

(For Institutional Use Only).

NDC 0054-2531-25: Bottles of 100 capsules.

Store and Dispense:

Store at 25°C (77°F); excursions permitted to 15 to 30°C (59 to 86°F) [see USP Controlled Room Temperature]. Protect from moisture. Dispense in a tight container as defined in the USP/NF.

Lithium Oral Solution USP, 8 mEq per 5 mL.

NDC 0054-8529-04: Unit dose Patient Cup™ filled to deliver 5 mL, ten 5 mL Patient Cup™ per shelf pack, ten shelf packs per shipper.

(For Institutional Use Only).

NDC 0054-3527-63: Bottles of 500 mL.

Store and Dispense:

Store at 25°C (77°F); excursions permitted to 15 to 30°C (59 to 86°F) [see USP Controlled Room Temperature]. Dispense in a tight container as defined in the USP/NF.

4055500//08

Revised October 2011

© RLI, 2011

Package Label - Lithium Carbonate Tablets USP